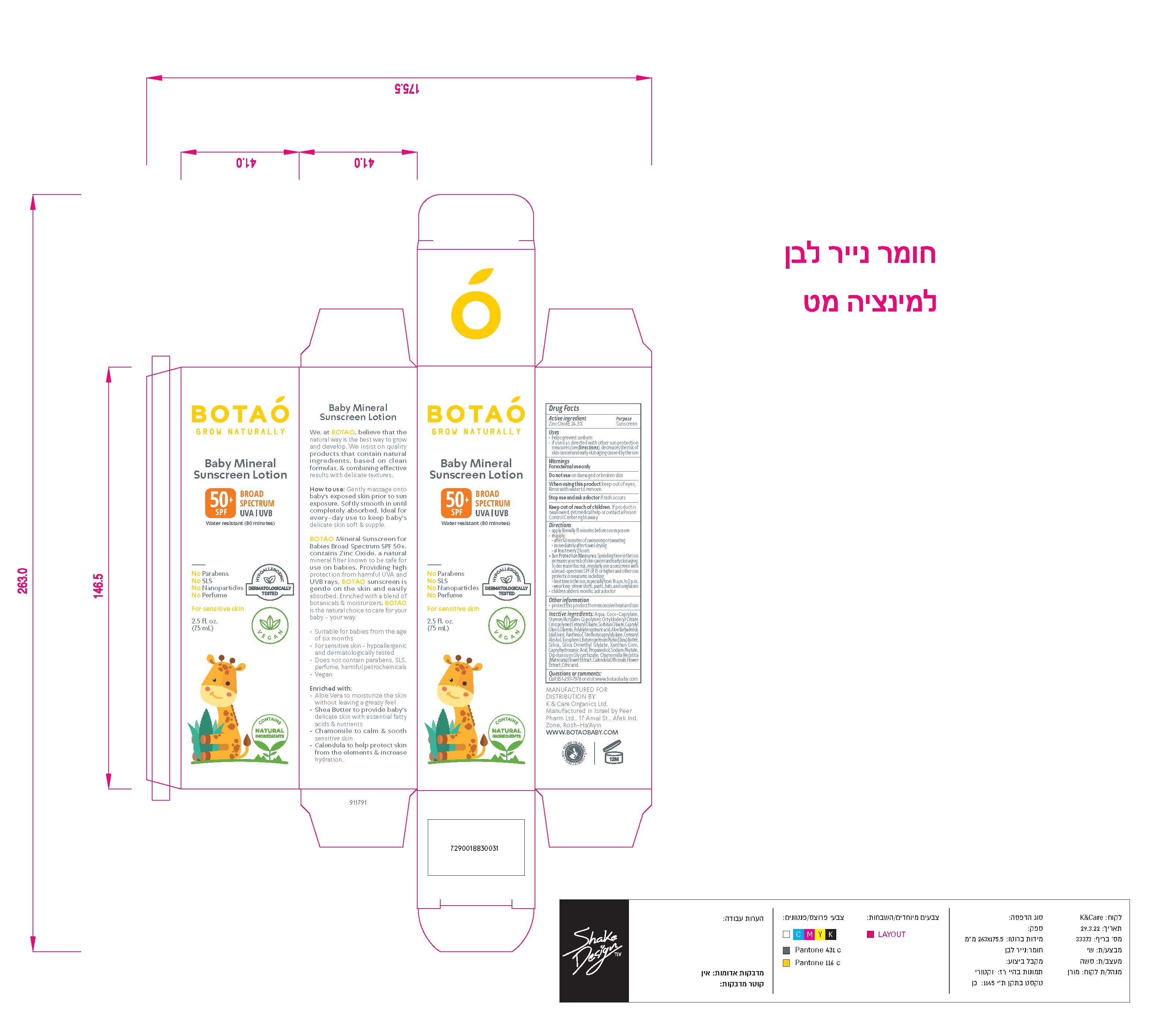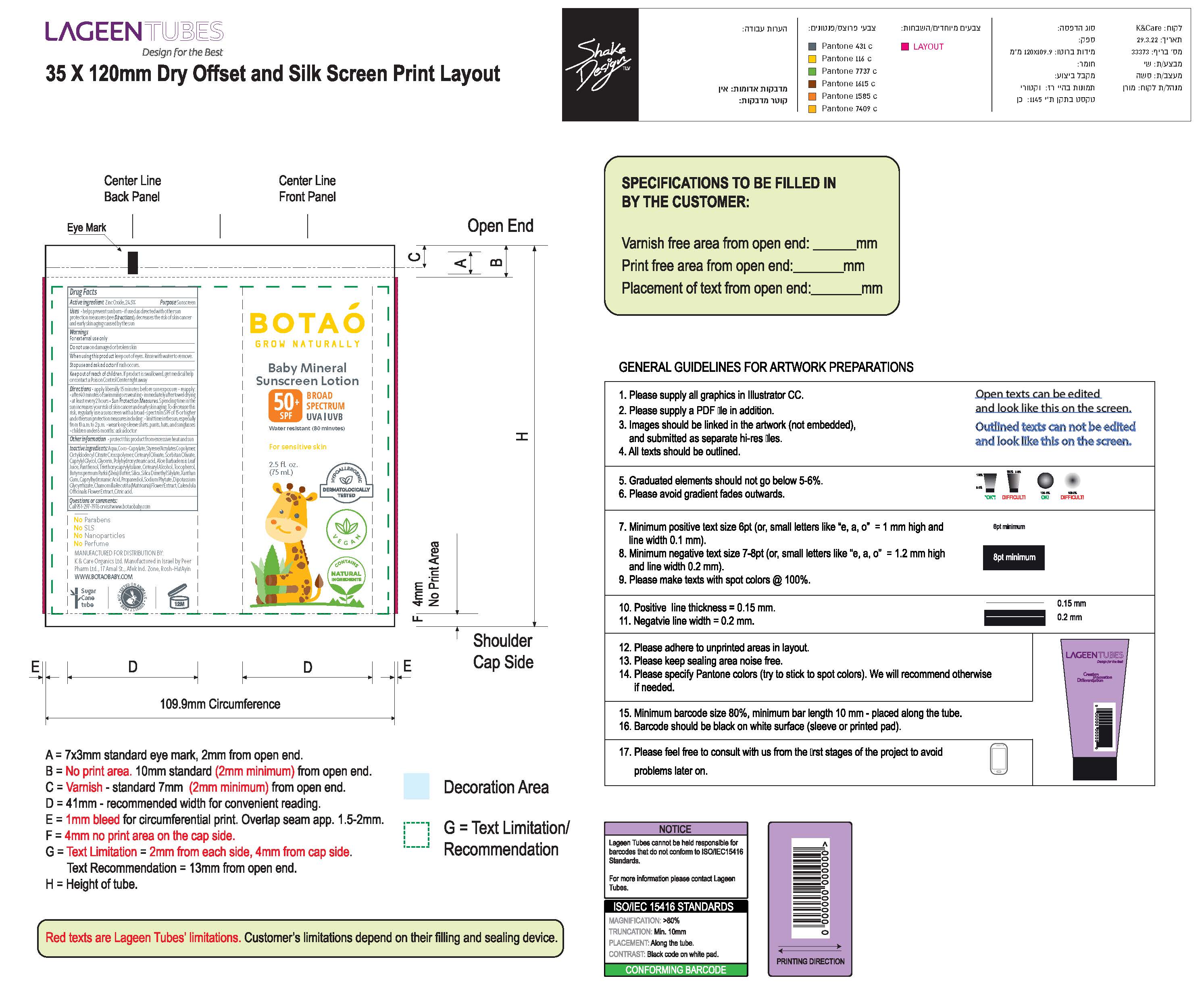 DRUG LABEL: Botao Baby Mineral Sunscreen L
NDC: 69435-1504 | Form: LOTION
Manufacturer: Peer Pharm Ltd.
Category: otc | Type: HUMAN OTC DRUG LABEL
Date: 20260112

ACTIVE INGREDIENTS: ZINC OXIDE 17 g/66 g
INACTIVE INGREDIENTS: TOCOPHEROL; CITRIC ACID ISOPROPYL ETHER; CETEARYL ETHYLHEXANOATE; HEXASODIUM PHYTATE; CALENDULA OFFICINALIS SEED OIL; TRIETHOXYCAPRYLYLSILANE; SHEA BUTTER; SILICA DIMETHYL SILYLATE; XANTHAN GUM; CAPRYLHYDROXAMIC ACID; DIPOTASSIUM GLUCOSE-6-PHOSPHATE; POLYHYDROXYSTEARIC ACID (2300 MW); CAPRYLYL GLYCOL; COCO-CAPRYLATE; SODIUM ACRYLATE/STYRENE SULFONATE COPOLYMER (11000 MW); ISOBUTANE; WATER; 1-(ETHYLTRISULFANYL)PROPANE; TRIOCTYLDODECYL CITRATE; ACRYLATES CROSSPOLYMER-4; CETEARYL OLIVATE; SORBITAN OLIVATE; CASTOR OIL; GLYCERIN; PROPANEDIOL 1-PHOSPHATE; CHAMOMILE; PANTHENOL; ALOE; 1,4-BUTANEDITHIOL

Botao Baby Mineral Sunscreen Lotion SPF 50

Active Ingredients(in each 30 ml)

Zinc Oxide 24.5%

Purpose

Sunscreen

Uses

- Helps prevent sunburn
- if used as directed with other sun protection measures (see Directions), decreases the risk of skin cancer and early skin aging caused by the sun.

warnings

- For external use only.

Do not use

- on damaged or broken skin.

When using this product,

- Keep out of eyes. Rinse with water to remove.

Stop use and ask a doctor

- if rash or irritation develops and lasts.

Keep out of reach of children.

If swallowed, call a poison control center or get medical help right away.

Directions

shake well before each use

spray liberally and spread evenly by hand 15 minutes before sun exposure

hold4 to 6 inches from the skin to apply

do not spray directly into face.

Spray on hands then apply to face

do not apply in windy conditions

Use in a well-ventilated area

reapply: after 40 minutes of swimming or sweating

immediately after towel drying

at least every 2 hours

Inactive Ingredients

Water,Coco-Caprylate, Styrene/Acrylates Copolymer,Butane,Isobutane, Propane, Octlydodecyl Citrate Crosspolymer,Cetearyl Olivate, Sorbitan Olivate, Caprylyl Glycol, Glycerin, Polyhydroxystearic acid, Aloe Barbadensis Leaf Juice, Panthenol, Triethoxycapryllsilane, Cetearyl Alcohol,Tocopherol, Butyrosperum Parkii (Shea) Butter,Silica, Silica Dimethyl Silyate , Xanthan Gum, Caprylhydroxamix Acid, Propanediol, Sodium Phytate, Dipotassium Glycyrrhizate, Chamomilla Recutita, (Matricaria) Flower Extract ,Calendula Officianlis Flower Extract,Citric Acid

Other Information

- Store in room temparture
- protect from freezing
- may stain clothing